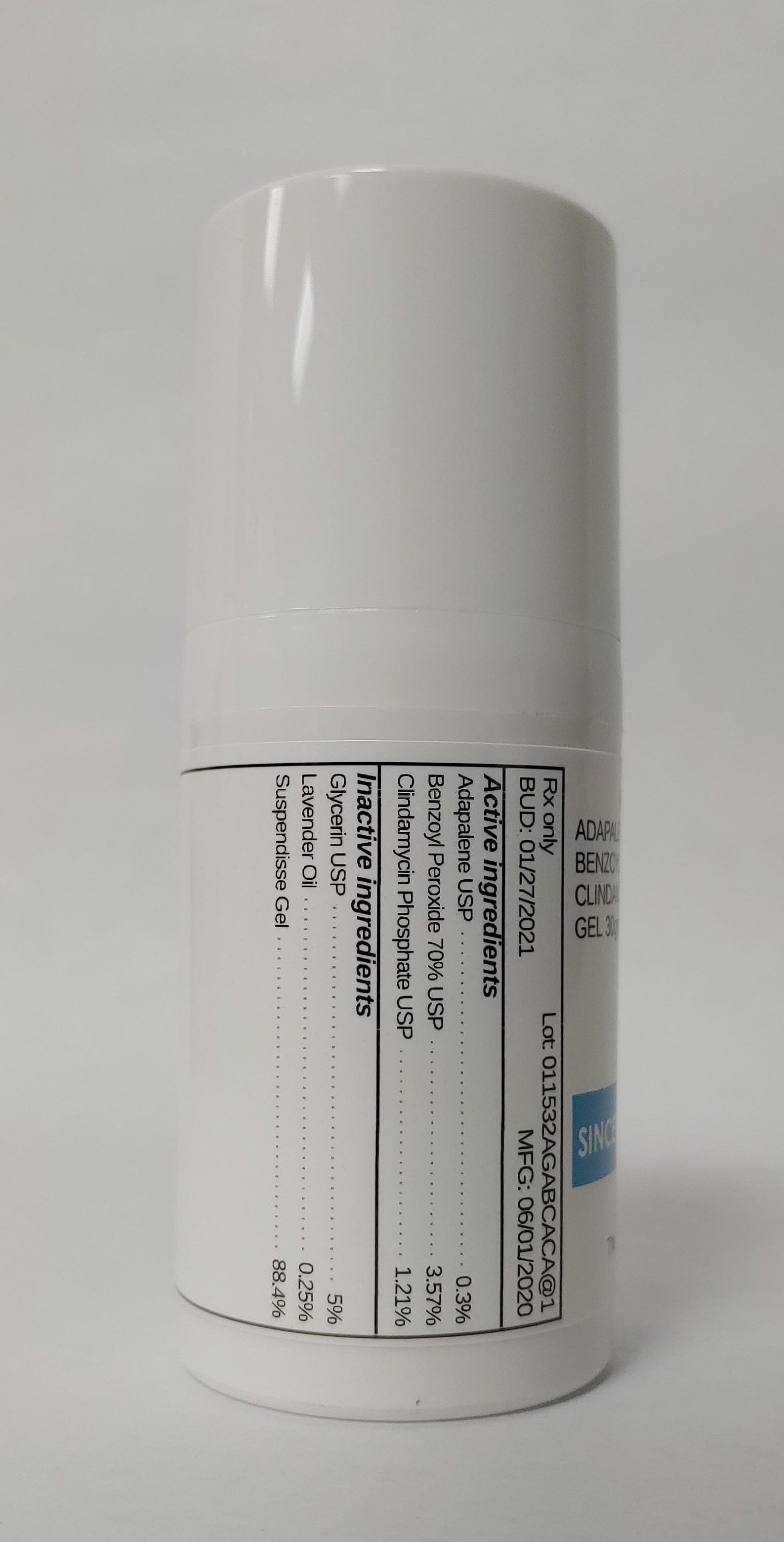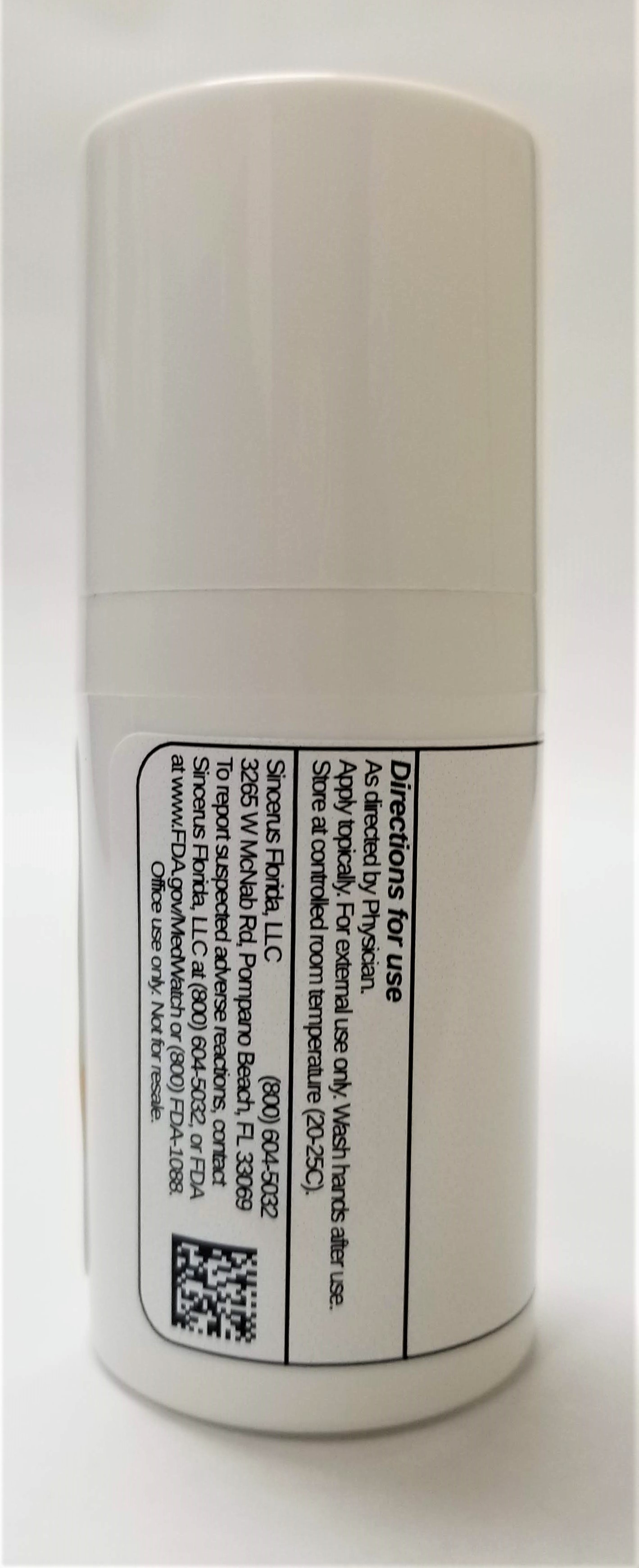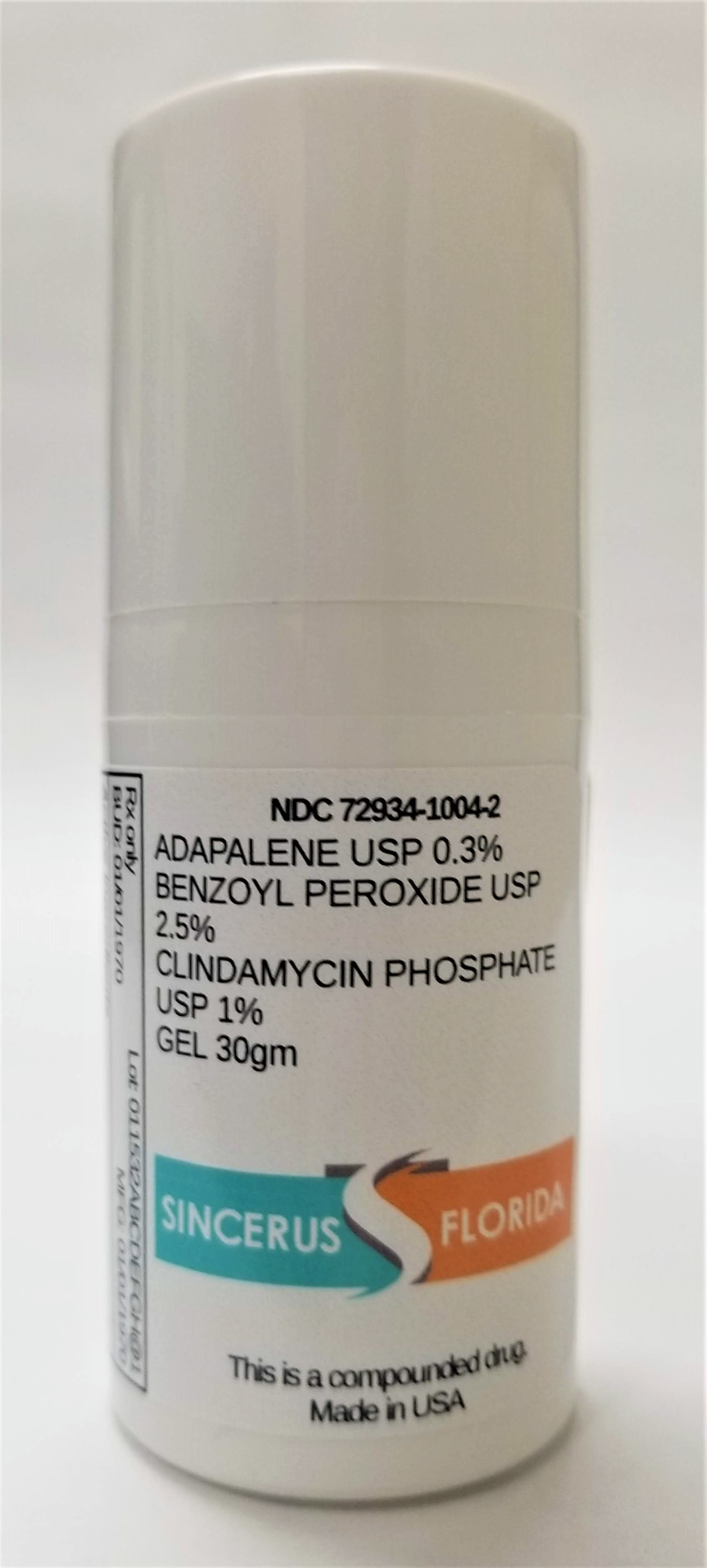 DRUG LABEL: ADAPALENE 0.3% / BENZOYL PEROXIDE 2.5% / CLINDAMYCIN 1%
NDC: 72934-1004 | Form: GEL
Manufacturer: Sincerus Florida, LLC
Category: prescription | Type: HUMAN PRESCRIPTION DRUG LABEL
Date: 20200603

ACTIVE INGREDIENTS: CLINDAMYCIN PHOSPHATE 1 g/100 g; ADAPALENE 0.3 g/100 g; BENZOYL PEROXIDE 2.5 g/100 g

ADAPALENE 0.3% / BENZOYL PEROXIDE 2.5% / CLINDAMYCIN 1%